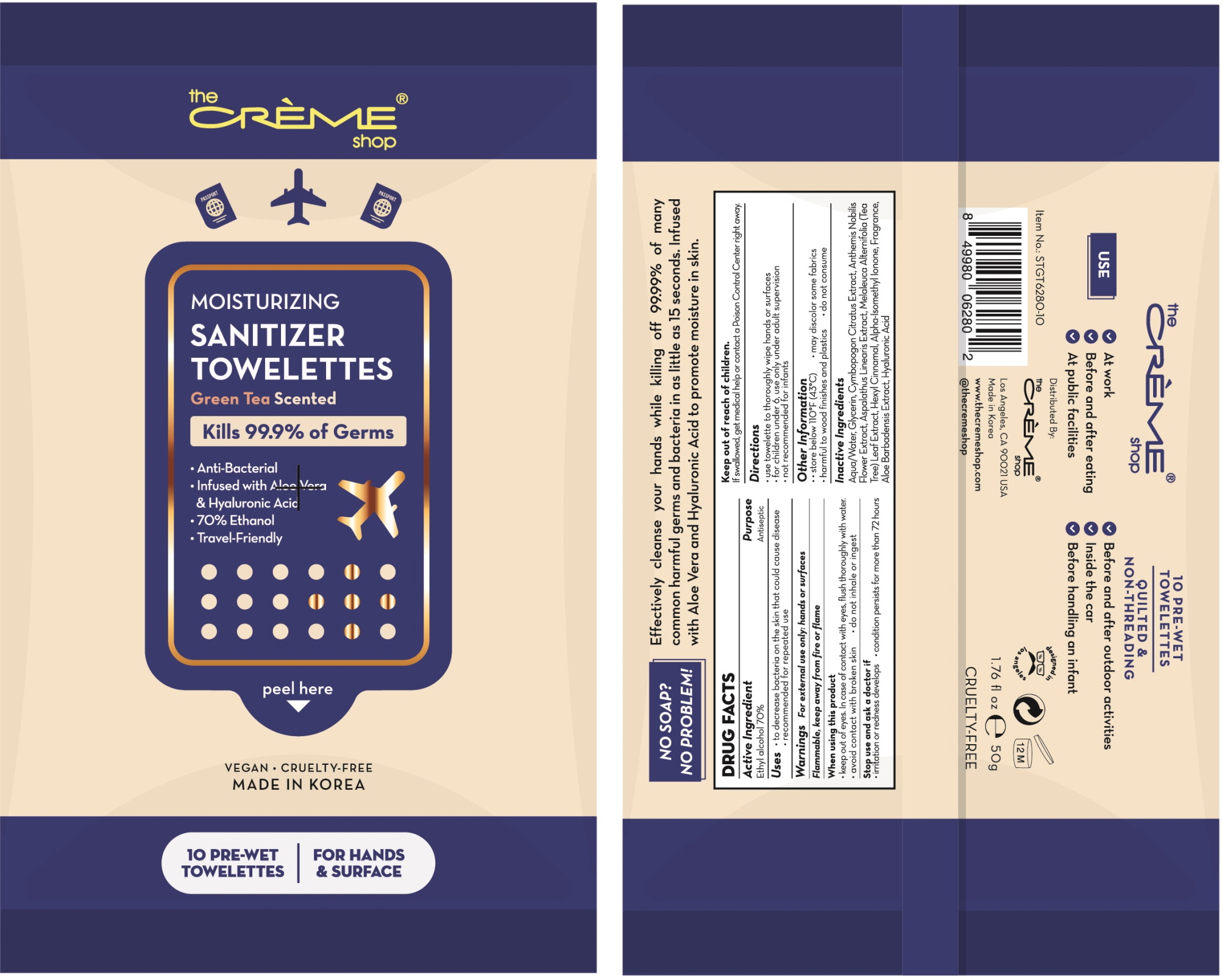 DRUG LABEL: MOISTURIZING SANITIZER TOWELETTES GREEN TEA
NDC: 75010-090 | Form: CLOTH
Manufacturer: Mirfeel Korea Co., Ltd
Category: otc | Type: HUMAN OTC DRUG LABEL
Date: 20200619

ACTIVE INGREDIENTS: Alcohol 0.70 1/1 1
INACTIVE INGREDIENTS: Water; Glycerin; CHAMAEMELUM NOBILE FLOWER; MELALEUCA ALTERNIFOLIA LEAF; .ALPHA.-HEXYLCINNAMALDEHYDE; ISOMETHYL-.ALPHA.-IONONE; ALOE VERA LEAF; Hyaluronic Acid

ACTIVE INGREDIENT

Ethyl alcohol 70%

INACTIVE INGREDIENT

Aqua/Water, Glycerin, Cymbopogon Citratus Extract, Anthemis Nobilis Flower Extract, Aspalathus Linearis Extract, Melaleuca Alternifolia (Tea Tree) Leaf Extract, Hexyl Cinnamal, Alpha-Isomethyl Ionone, Fragrance, Aloe Barbadensis Extract, Hyaluronic Acid

PURPOSE

Antiseptic

WARNINGS

For external use only: hands

--------------------------------------------------------------------------------------------------------

Flammable. Keep away from fire or flame
--------------------------------------------------------------------------------------------------------
When using this product

ㆍkeep out of eyes. In case of contact with eyes, flush thoroughly with water.
ㆍavoid contact with broken skin ㆍdo not inhale or ingest
--------------------------------------------------------------------------------------------------------
Stop use and ask a doctor if

ㆍirritation or redness develops ㆍcondition persists for more than 72 hours

KEEP OUT OF REACH OF CHILDREN

If swallowed, get medical help or contact a Poison Control Center right away.

Uses

ㆍto decrease bacteria on the skin that could cause disease
ㆍrecommended for repeated use

Directions

ㆍuse towelette to throughly wipe hands or surfaces
ㆍfor children under 6, use only under adult supervision
ㆍnot recommended for infants

Other Information

ㆍstore below 110℉ (43℃) ㆍmay discolor some fabrics
ㆍharmful to wood finishes and plastics